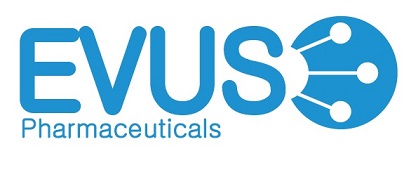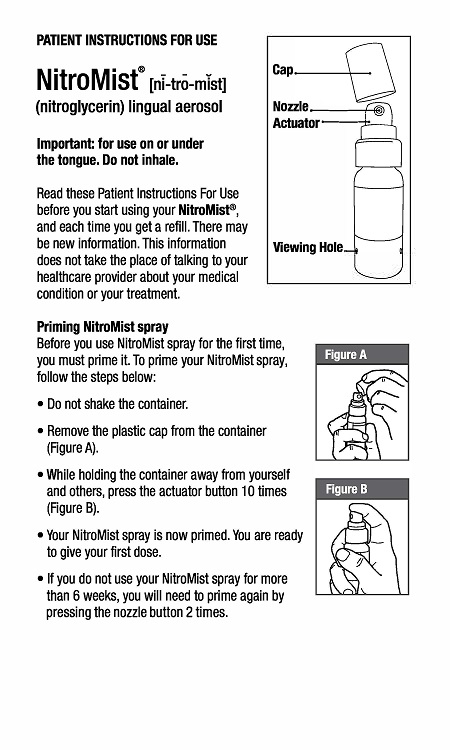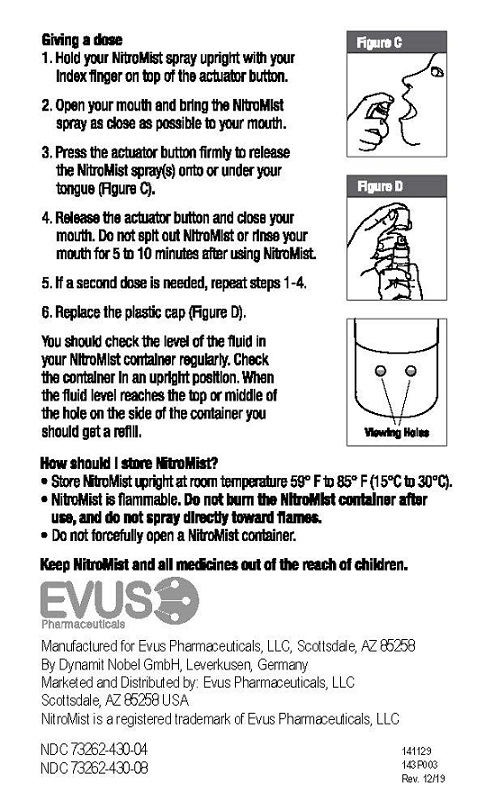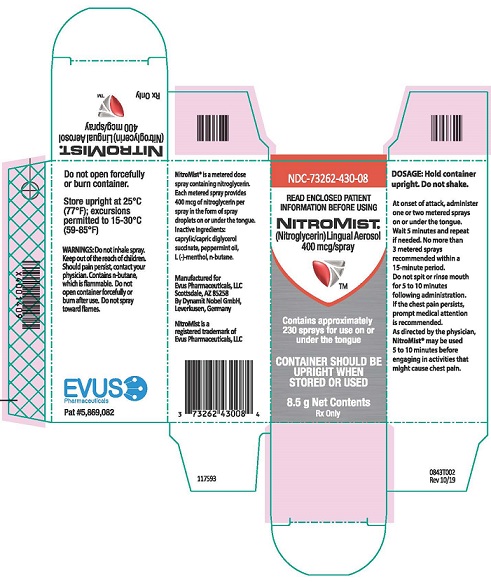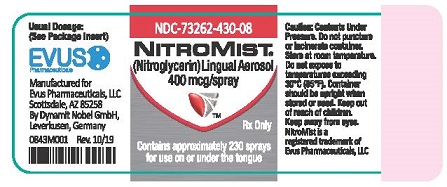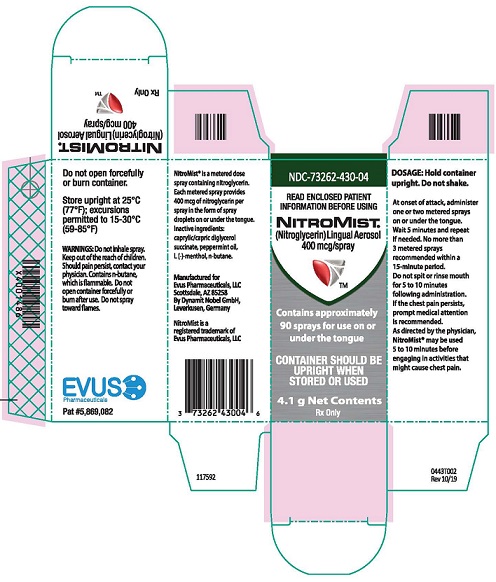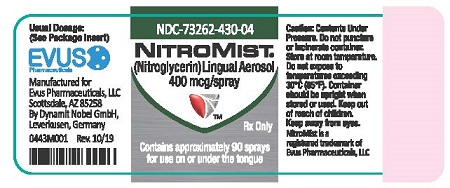 DRUG LABEL: NitroMist
NDC: 73262-430 | Form: AEROSOL, METERED
Manufacturer: Evus Pharmaceuticals, LLC
Category: prescription | Type: HUMAN PRESCRIPTION DRUG LABEL
Date: 20200608

ACTIVE INGREDIENTS: NITROGLYCERIN 400 ug/1 1
INACTIVE INGREDIENTS: CAPRYLIC/CAPRIC/SUCCINIC TRIGLYCERIDE; PEPPERMINT OIL; MENTHOL; BUTANE

HIGHLIGHTS OF PRESCRIBING INFORMATION

These highlights do not include all the information needed to use NitroMist safely and effectively. See full prescribing information for NitroMist.
NitroMist® (nitroglycerin) lingual aerosol
Initial U.S. Approval: 2006

1 INDICATIONS AND USAGE

NitroMist® is a nitrate vasodilator indicated for acute relief of an attack or acute prophylaxis of angina pectoris due to coronary artery disease (1).

2 DOSAGE AND ADMINISTRATION

- At the onset of an attack, one metered spray or two metered sprays should be administered on or under the tongue. A spray may be repeated approximately every 5 minutes as needed (2).
- Maximum of 3 metered sprays are recommended within a 15-minute period. If chest pain persists after a total of 3 sprays, prompt medical attention is recommended (2).
- May be used prophylactically 5 minutes to 10 minutes before engaging in activities that might precipitate an acute attack (2).

3 DOSAGE FORMS AND STRENGTHS

Lingual aerosol, 400 mcg per spray is available in either 230 metered sprays or 90 metered sprays per container (3)

4 CONTRAINDICATIONS

- Use of a selective inhibitor of cyclic guanosine monophosphate (cGMP)-specific phosphodiesterase type 5 (PDE5 inhibitors), such as sildenafil, vardenafil, and tadalafil (4.1)
- Use of the soluble guanylate stimulator riociguat (4.1)
- Severe anemia (4.2)
- Increased intracranial pressure (4.3)
- History of hypersensitivity to NitroMist or to other nitrates or nitrites (4.4)

5 WARNINGS AND PRECAUTIONS

- Tolerance: Excessive use may lead to tolerance (5.1).

6 ADVERSE REACTIONS

Most common adverse reactions are headache, flushing, hypotension, and syncope (6).

To report SUSPECTED ADVERSE REACTIONS, contact Evus Pharmaceuticals at 1-866-928-6180 or FDA at 1-800-FDA-1088 or www.fda.gov/medwatch/report.htm.

7 DRUG INTERACTIONS

- PDE5 inhibitors: Concomitant use contraindicated (4.1, 7.1)
- Soluble guanylate cyclase stimulator (sGS): Concomitant use contraindicated (4.1, 7.1)
- Antihypertensives: Possible additive hypotensive effects (7.2)
- Aspirin: increased nitroglycerin levels (7.3)
- Tissue-type plasminogen activator (t-PA): decreased thrombolytic effect (7.4)
- Heparin: anticoagulant effect of heparin may be reduced. Monitor APTT. (7.5)
- Ergotamine: increased bioavailability of ergotamine. Avoid concomitant use. (7.6)

FULL PRESCRIBING INFORMATION

1 INDICATIONS AND USAGE

NitroMist is indicated for acute relief of an attack or acute prophylaxis of angina pectoris due to coronary artery disease.

2 DOSAGE AND ADMINISTRATION

2.1 Recommended Dosage

At the onset of an attack, one metered spray or two metered sprays should be administered on or under the tongue. A spray may be repeated approximately every 5 minutes as needed. If two sprays are used initially, the patient may only administer one more spray after waiting 5 minutes. No more than 3 metered sprays are recommended within a 15-minute period. If chest pain persists after a total of 3 sprays, prompt medical attention is recommended. NitroMist may be used prophylactically 5 minutes to 10 minutes before engaging in activities that might precipitate an acute attack.

2.2 Priming the Container

After an initial priming of 10 sprays, each metered spray of NitroMist delivers 33 mg of solution containing 400 mcg of nitroglycerin. It will remain adequately primed for 6 weeks. If the product is not used within 6 weeks, it can be adequately re-primed with 2 sprays. NitroMist is available in either 230 metered sprays or 90 metered sprays per container, but the total number of available doses depends on the number of sprays per use (1 spray or 2 sprays), and the frequency of priming.

2.3 Administration

During use the patient should rest, ideally in the sitting position. The container should be held vertically with the valve head uppermost and the spray orifice as close to the mouth as possible. The dose should preferably be sprayed into the mouth on or under the tongue by pressing the button firmly and the mouth should be closed immediately after each dose. THE SPRAY SHOULD NOT BE INHALED. Patients should be instructed to familiarize themselves with the position of the spray orifice, which can be identified by the finger rest on top of the valve, in order to facilitate orientation for administration at night.

1. Do not shake container.
2. Remove plastic cap.
3. If this is the first time using the bottle, press actuator button 10 times to ensure proper dose priming (holding unit away from yourself and others).
4. Hold container upright with forefinger on top of the actuator button.
5. Open mouth and bring the container as close as possible.
6. Press the actuator button firmly with forefinger to release spray(s) onto or under the tongue.
7. Release button and close mouth. The medication should not be spit out or the mouth rinsed for 5 minutes to 10 minutes following administration.
8. If a second administration is required to obtain relief, repeat steps 4, 5, and 6. No more than 3 metered sprays can be given within a 15-minute period.
9. Replace plastic cover.
10. If the product is not used for more than 6 weeks, then it can be adequately re-primed with 2 sprays.

The level of the liquid in the container should be periodically checked. While the container is in the upright position, if the liquid reaches the top or middle of the hole on the side of the container, one should order more. When the liquid reaches the bottom of the hole, the remaining doses will have less than label content.

3 DOSAGE FORMS AND STRENGTHS

Lingual aerosol, 400 mcg per spray, is available in either 230 metered sprays or 90 metered sprays per container.

4 CONTRAINDICATIONS

4.1 PDE5 Inhibitor Use

Administration of NitroMist is contraindicated in patients who are using a selective inhibitor of cyclic guanosine monophosphate (cGMP)-specific phosphodiesterase type 5 (PDE5), as PDE5 inhibitors such as sildenafil, vardenafil, and tadalafil have been shown to potentiate the hypotensive effects of organic nitrates. Do not use NitroMist in patients who are taking the soluble guanylate cyclase (sGC) stimulator riociguat. Concomitant use can cause hypotension. [see DRUG INTERACTIONS (7.1)].

4.2 Severe Anemia

NitroMist is contraindicated in patients with severe anemia.

4.3 Increased Intracranial Pressure

NitroMist is contraindicated in patients with increased intracranial pressure.

4.4 Hypersensitivity

NitroMist is contraindicated in patients who have shown hypersensitivity to it or to other nitrates or nitrites. Skin reactions consistent with hypersensitivity have been observed with organic nitrates.

5 WARNINGS AND PRECAUTIONS

5.1 Tolerance

Excessive use may lead to the development of tolerance. Only the smallest number of doses required for effective relief of the acute anginal attack should be used [see DOSAGE AND ADMINISTRATION (2)].

As tolerance to other forms of nitroglycerin develops, the effect of sublingual nitroglycerin on exercise tolerance, although still observable, is reduced.

5.2 Hypotension

Severe hypotension, particularly with upright posture, may occur even with small doses of nitroglycerin. The drug should therefore be used with caution in patients who may be volume-depleted or who, for whatever reason, are already hypotensive. Hypotension induced by nitroglycerin may be accompanied by paradoxical bradycardia and increased angina pectoris.

The benefits of NitroMist in patients with acute myocardial infarction or congestive heart failure have not been established. If one elects to use NitroMist in these conditions, careful clinical or hemodynamic monitoring must be used because of the possibility of hypotension and tachycardia.

5.3 Hypertrophic Cardiomyopathy

Nitrate therapy may aggravate the angina caused by hypertrophic cardiomyopathy.

5.4 Headache

Nitroglycerin produces dose-related headaches, which may be severe. Tolerance to headaches occurs.

6 ADVERSE REACTIONS

6.1 Headache

Headache, which may be severe and persistent, may occur immediately after nitroglycerin use.

6.2 Flushing

Flushing, drug rash and exfoliative dermatitis have been reported in patients receiving nitrate therapy.

6.3 Hypotension

Postural hypotension, as manifest by vertigo, weakness, palpitation, and other symptoms, may develop occasionally, particularly in erect, immobile patients. Marked sensitivity to the hypotensive effects of nitrates (manifested by nausea, vomiting, weakness, diaphoresis, pallor, and collapse) may occur at therapeutic doses.

6.4 Syncope

Syncope due to nitrate vasodilatation has been reported.

7 DRUG INTERACTIONS

7.1 PDE5 Inhibitors

Administration of NitroMist is contraindicated in patients who are using a selective inhibitor of cyclic guanosine monophosphate (cGMP)-specific phosphodiesterase type 5 (PDE5). PDE5 inhibitors such as sildenafil, vardenafil, and tadalafil have been shown to potentiate the hypotensive effects of organic nitrates. Do not use NitroMist in patients who are taking the soluble guanylate cyclase (sGC) stimulator riociguat. Concomitant use may result in severe hypotension, syncope, or myocardial ischemia.

The time course and dose dependence of this interaction have not been studied, and use within a few days of one another cannot be recommended. Appropriate supportive care for the severe hypotension has not been studied, but it seems reasonable to treat this as a nitrate overdose, with elevation of the extremities and with central volume expansion. The use of any form of nitroglycerin during the early days of acute myocardial infarction requires particular attention to hemodynamic monitoring and clinical status.

7.2 Antihypertensives

Patients receiving antihypertensive drugs, beta-adrenergic blockers, and nitrates should be observed for possible additive hypotensive effects. Marked orthostatic hypotension has been reported when calcium channel blockers and organic nitrates were used concomitantly.

Labetolol blunts the reflex tachycardia produced by nitroglycerin without preventing its hypotensive effects. If labetolol is used with nitroglycerin in patients with angina pectoris, additional hypotensive effects may occur.

7.3 Aspirin

Coadministration of aspirin and nitroglycerin has been reported to result in increased nitroglycerin maximum concentrations by as much as 67% and AUC by 73% when administered as a single dose. The vasodilatory and hemodynamic effects of nitroglycerin may be enhanced by concomitant administration of aspirin.

7.4 Tissue-type Plasminogen Activator (t-PA)

Intravenous administration of nitroglycerin decreases the thrombolytic effect of tissue-type plasminogen activator (t-PA). Plasma levels of t-PA are reduced when coadministered with nitroglycerin. Therefore, caution should be observed in patients receiving nitroglycerin during t-PA therapy.

7.5 Heparin

Intravenous nitroglycerin reduces the anticoagulant effect of heparin. Activated partial thromboplastin times (APTT) should be monitored in patients receiving heparin and intravenous nitroglycerin. It is not known if this effect occurs following single nitroglycerin doses.

7.6 Ergotamine

Oral administration of nitroglycerin markedly decreases the first-pass metabolism of dihydroergotamine and subsequently increases its oral bioavailability. Ergotamine is known to precipitate angina pectoris. Therefore, patients receiving sublingual nitroglycerin should avoid ergotamine and related drugs or be monitored for symptoms of ergotism if this is not possible.

8 USE IN SPECIFIC POPULATIONS

8.1 Pregnancy

Risk Summary

Limited published data on the use of nitroglycerin are insufficient to determine a drug associated risk of major birth defects or miscarriage. In animal reproduction studies, there were no adverse developmental effects when nitroglycerin was administered intravenously to rabbits or intraperitoneally to rats during organogenesis at doses greater than 64-times the human dose [see Data].

The estimated background risk of major birth defects and miscarriage for the indicated population is unknown. In the U.S. general population, the estimated background risk of major birth defects and miscarriage in clinically recognized pregnancies is 2 – 4% and 15 – 20%, respectively.

Data

Animal Data

No embryotoxic or postnatal development effects were observed with transdermal application in pregnant rabbits and rats at doses up to 240 mg/kg/day for 13 days, at intraperitoneal doses in pregnant rats up to 20 mg/kg/day for 11 days, and at intravenous doses in pregnant rabbits up to 4 mg/kg/day for 13 days.

8.2 Lactation

Risk Summary

Sublingual nitroglycerin has not been studied in lactating women. It is not known if nitroglycerin is present in human milk, or if nitroglycerin has effects on milk production or the breastfed child. Therefore, the developmental and health benefits of breastfeeding should be considered along with the mother’s need for nitroglycerin and any potential adverse effects on the breastfed child from nitroglycerin or from the underlying maternal condition.

8.3 Pediatric Use

The safety and effectiveness of nitroglycerin in pediatric patients have not been established.

8.4 Geriatric Use

Clinical studies of NitroMist did not include sufficient numbers of subjects aged 65 and over to determine whether they respond differently from younger subjects. Other reported clinical experience has not identified differences in responses between elderly (greater than or equal to 65 years) and younger (less than 65 years) patients. In general, dose selection for an elderly patient should be cautious, usually starting at the low end of the dosing range, reflecting the greater frequency of decreased hepatic, renal, or cardiac function, and of concomitant disease or other drug therapy.

10 OVERDOSAGE

Signs and symptoms of hemodynamic effects: The effects of nitroglycerin overdose are generally the results of nitroglycerin’s capacity to induce vasodilatation, venous pooling, reduced cardiac output, and hypotension. These hemodynamic changes may have protean manifestations, including increased intracranial pressure with any or all of persistent throbbing headache, confusion, and moderate fever; vertigo; palpitations; tachycardia; visual disturbances; nausea and vomiting (possibly with colic and even bloody diarrhea); syncope (especially in the upright posture); dyspnea, later followed by reduced ventilatory effort, diaphoresis, with the skin either flushed or cold and clammy; heart block and bradycardia; paralysis; coma; seizures; and death.

No specific antagonist to the vasodilator effects of nitroglycerin is known, and no intervention has been subject to controlled study as a therapy of nitroglycerin overdose. Because the hypotension associated with nitroglycerin overdose is the result of venodilatation and arterial hypovolemia, prudent therapy in this situation should be directed toward increase in central fluid volume. Passive elevation of the patient’s legs may be sufficient, but intravenous infusion of normal saline or similar fluid may also be necessary.

The use of epinephrine or other arterial vasoconstrictors in this setting is not recommended.

In patients with renal disease or congestive heart failure, therapy resulting in central volume expansion is not without hazard. Treatment of nitroglycerin overdose in these patients may be subtle and difficult, and invasive monitoring may be required.

Methemoglobinemia: Methemoglobinemia has been rarely reported with organic nitrates. The diagnosis should be suspected in patients who exhibit signs of impaired oxygen delivery despite adequate arterial PO2. Classically, methemoglobinemic blood is described as chocolate brown, without color change on exposure to air.

If methemoglobinemia is present, intravenous administration of methylene blue, 1 mg/kg to 2 mg/kg of body weight, may be required.

11 DESCRIPTION

Nitroglycerin, an organic nitrate, is a vasodilator which has effects on both arteries and veins. The chemical name for nitroglycerin is 1,2,3-propanetriol trinitrate (C3H5N3O9). The compound has a molecular weight of 227.09. The chemical structure is:

CH2 – ONO2

|

CH – ONO2

|

CH2 – ONO2

NitroMist (nitroglycerin) lingual aerosol is a metered-dose spray containing 230 metered sprays or 90 metered sprays of nitroglycerin per container. This product delivers 400 mcg of nitroglycerin per actuation in the form of spray droplets on or under the tongue. Inactive ingredients: caprylic/capric diglycerol succinate, peppermint oil, L(-)-menthol, n-butane.

12 CLINICAL PHARMACOLOGY

12.1 Mechanism of Action

Nitroglycerin forms free radical nitric oxide (NO), which activates guanylate cyclase, resulting in an increase of guanosine 3’,5’-monophosphate (cyclic GMP) in smooth muscle and other tissues. This eventually leads to dephosphorylation of myosin light chains, which regulates the contractile state in smooth muscle and results in vasodilatation.

12.2 Pharmacodynamics

The principal pharmacological action of nitroglycerin is relaxation of vascular smooth muscle. Although venous effects predominate, nitroglycerin produces, in a dose-related manner, dilation of both arterial and venous beds. Dilation of the postcapillary vessels, including large veins, promotes peripheral pooling of blood, decreases venous return to the heart, and reduces left ventricular end-diastolic pressure (preload). Nitroglycerin also produces arteriolar relaxation, thereby reducing peripheral vascular resistance and arterial pressure (after load), and dilates large epicardial coronary arteries; however, the extent to which this latter effect contributes to the relief of exertional angina is unclear.

Therapeutic doses of nitroglycerin may reduce systolic, diastolic and mean arterial blood pressure. Effective coronary perfusion pressure is usually maintained, but can be compromised if blood pressure falls excessively or increased heart rate decreases diastolic filling time.

Elevated central venous and pulmonary capillary wedge pressures, and pulmonary and systemic vascular resistance are also reduced by nitroglycerin therapy. Heart rate is usually slightly increased, presumably a reflex response to the fall in blood pressure. Cardiac index may be increased, decreased, or unchanged. Myocardial oxygen consumption or demand (as measured by the pressure-rate product, tension-time index, and stroke-work index) is decreased and a more favorable supply-demand ratio can be achieved. Patients with elevated left ventricular filling pressure and increased systemic vascular resistance in association with a depressed cardiac index are likely to experience an improvement in cardiac index. In contrast, when filling pressures and cardiac index are normal, cardiac index may be slightly reduced following nitroglycerin administration.

12.3 Pharmacokinetics

Nitroglycerin is rapidly absorbed following lingual spray administration. In a pharmacokinetic study when a single 1200 mcg dose (three activations of a 400 mcg dose) of NitroMist was administered to healthy volunteers (n=12), all subjects had detectable trinitroglycerin plasma levels (mean Cmax 0.8 ng/mL ± 0.7 ng/mL and tmax of 8 minutes, range 4 minutes to 15 minutes) beginning at 2 minutes post-dose and higher levels of the 1,2- (mean Cmax 3.7 ng/mL ± 1 ng/mL and tmax 34 minutes ± 21 minutes, range 15 minutes to 90 minutes) and 1,3-dinitroglycerin metabolites (mean Cmax 1 ng/mL ± 0.3 ng/mL and mean tmax 41 minutes ± 20 minutes, range 20 minutes to 90 minutes).

The volume of distribution of nitroglycerin following intravenous administration is 3.3 L/kg.

A liver reductase enzyme is of primary importance in the metabolism of nitroglycerin to glycerol di- and mononitrate metabolites and ultimately to glycerol and organic nitrate. Known sites of extrahepatic metabolism include red blood cells and vascular walls. In addition to nitroglycerin, 2 major metabolites, 1,2- and 1,3-dinitroglycerin are found in plasma. The mean elimination half-life of both 1,2- and 1,3-dinitroglycerin is about 40 minutes. The 1,2- and 1,3-dinitroglycerin metabolites have been reported to possess some pharmacological activity, whereas the glycerol mononitrate metabolites of nitroglycerin are essentially inactive. Higher plasma concentrations of the dinitro metabolites, with their nearly 8-fold longer elimination half-lives, may contribute significantly to the duration of pharmacologic effect.

In the above referenced pharmacokinetic study the average initial half-lives (T½α) of nitroglycerin, and its 1,2- and 1,3-dinitroglycerin metabolites were estimated to be 3 minutes, 10 minutes, and 11 minutes, respectively. The half-life of disappearance of the nitroglycerin (T½β) (5 minutes) was significantly less than the half-life of appearance (T½α) of the 1,2- and 1,3-dinitroglycerin metabolites suggesting the possibility of an additional compartment into which the nitroglycerin disappears from plasma prior to being metabolized into the dinitroglycerin metabolites. A second indication of this other compartment is that the appearance of nitroglycerin metabolites in plasma was delayed in some subjects, with zero plasma levels seen for 4 minutes to 6 minutes after dosing. In some subjects, nitroglycerin metabolites appeared only after nitroglycerin Cmax had been observed.

13 NONCLINICAL TOXICOLOGY

13.1 Carcinogenesis, Mutagenesis, Impairment of Fertility

Animal carcinogenicity studies with sublingually administered or lingual spray nitroglycerin have not been performed.

Rats receiving up to 434 mg/kg/day of dietary nitroglycerin for 2 years developed dose-related fibrotic and neoplastic changes in liver, including carcinomas, and interstitial cell tumors in testes. At the highest dose, the incidences of hepatocellular carcinomas was 52% compared to 0% in untreated controls. Incidences of testicular tumors were 52% vs 8% in controls. Lifetime dietary administration of up to 1058 mg/kg/day of nitroglycerin was not tumorigenic in mice.

Nitroglycerin was found to have reverse mutation activity in the Salmonella typhimurium strain TA1535 (Ames assay). A similar mutation in S. typhimurium strain was also reported for other NO donors. Nevertheless, there was no evidence of mutagenicity in an in vivo dominant lethal assay with male rats treated with oral doses of up to about 363 mg/kg/day or in ex vitrocytogenic tests in rat and dog tissues. In vitro cytogenetic assay using Chinese hamster ovary cells showed no chromosomal aberrations.

In a 3-generation reproduction study, rats received dietary nitroglycerin at doses up to about 408 mg/kg/day (males) to 452 mg/kg/day (females) for 5 months (females) or 6 months (males) prior to mating of the F0 generation with treatment continuing through successive F1 and F2 generations. The highest dose was associated with decreased feed intake and body weight gain in both sexes at all matings. No specific effect on the fertility of the F0 generation was seen. Infertility noted in subsequent generations, however, was attributed to increased interstitial cell tissue and aspermatogenesis in the high-dose males.

14 CLINICAL STUDIES

In a randomized, double-blind, single-center, single-administration, placebo-controlled, 4-period cross-over study in 30 subjects with stable angina pectoris, statistically significant dose-related increases in exercise tolerance were seen following doses of 200 mcg, 400 mcg, and 800 mcg of nitroglycerin delivered by NitroMist compared to placebo.

16 HOW SUPPLIED/STORAGE AND HANDLING

Each box of NitroMist contains one glass bottle coated with red/orange transparent plastic which assists in containing the glass and medication should the bottle be shattered. NitroMist is available as an 8.5 g (Net Content) of nitroglycerin lingual aerosol that will deliver 230 metered sprays containing 400 mcg of nitroglycerin per actuation or as a 4.1 g (Net Content) of nitroglycerin lingual aerosol that will deliver 90 metered sprays containing 400 mcg of nitroglycerin per actuation.

230 metered sprays: NDC 73262-430-08
90 metered sprays: NDC 73262-430-04

- Storage
  Store at room temperature (25 °C, 77 °F); excursions permitted to 15 ° to 30 °C (59 ° to 85 °F)
- Handling
  NitroMist contains a highly flammable propellant (butane). Do not forcefully open a NitroMist bottle, do not have the container burned after use, and do not spray directly toward flames.

17 PATIENT COUNSELING INFORMATION

17.1 Interaction with PDE5 Inhibitors

NitroMist should not be used in patients who are using medications for erectile dysfunction such as sildenafil, vardenafil, and tadalafil. These products have been shown to increase the hypotensive effects of nitrate drugs such as NitroMist.

17.2 Administration

Patients should be instructed that prior to initial use of NitroMist Lingual aerosol, the pump must be primed by pressing the actuator button 10 times to ensure proper dose priming. If the product is not used for more than 6 weeks, the bottle can be adequately re-primed with 2 sprays.

NitroMist is meant to be sprayed on or under the tongue at the beginning of angina or to prevent an angina attack. Treatment with nitroglycerin products such as NitroMist may be associated with lightheadedness on standing, especially just after rising from a laying or seated position. This effect may be more frequent in patients who have consumed alcohol, since alcohol use contributes to hypotension. If possible, patients should be seated when taking NitroMist. This reduces the likelihood of falling due to lightheadedness or dizziness [ see DOSAGE AND ADMINISTRATION (2.3)].

17.3 Headache

Headaches can sometimes accompany treatment with nitroglycerin. In patients who get these headaches, the headaches may indicate activity of the drug. Tolerance to headaches develops.

17.4 Flushing

Flushing, drug rash and exfoliative dermatitis have been reported in patients receiving nitrate therapy.

17.5 Container information

The NitroMist bottle should not be forcefully opened. Because NitroMist contains a highly flammable propellant (butane), do not have the container burned after use and do not spray directly towards flames.

While the container is in the upright position, if the liquid reaches the top to middle of the hole on the side of the container, a new supply should be obtained. When the liquid reaches the bottom of the hole, the remaining doses will have less than label content .

Manufactured for Evus Pharmaceuticals, LLC
Scottsdale, AZ 85258 USA
by Dynamit Nobel GmbH, Leverkusen, Germany

Marketed and Distributed by: Evus Pharmaceuticals, LLC
Scottsdale, AZ 85258 USA

NitroMist is a registered trademark of Evus Pharmaceuticals

141110

143F003
Revised 09/2019

PRINCIPAL DISPLAY PANEL

NDC 73262-430-08
NITROMIST
(Nitroglycerin) Lingual Aerosol
400 mcg/spray
contains approximately
230 sprays for use on or
under the tongue

PRINCIPAL DISPLAY PANEL

NDC 73262-430-04

NITROMIST
(Nitroglycerin) Lingual Aerosol
400 mcg/spray
contains approximately
90 sprays for use on or
under the tongue